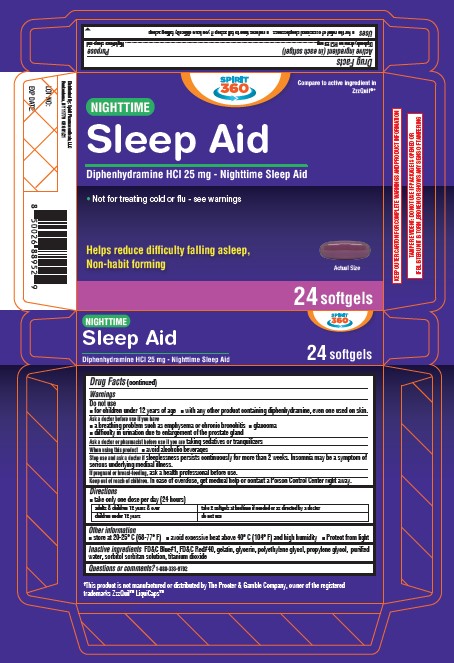 DRUG LABEL: Nighttime Sleep Aid
NDC: 68210-4195 | Form: CAPSULE, LIQUID FILLED
Manufacturer: Spirit Pharmaceuticals LLC
Category: otc | Type: HUMAN OTC DRUG LABEL
Date: 20241213

ACTIVE INGREDIENTS: DIPHENHYDRAMINE HYDROCHLORIDE 25 mg/1 1
INACTIVE INGREDIENTS: FD&C BLUE NO. 1; FD&C RED NO. 40; GELATIN; GLYCERIN; POLYETHYLENE GLYCOL, UNSPECIFIED; PROPYLENE GLYCOL; WATER; SORBITOL; SORBITAN; TITANIUM DIOXIDE

Nighttime Sleep Aid

Active Ingredient (in each tablet)

Diphenhydramine Hydrochloride 25 mg

Purpose

Nighttime sleep-aid

Uses

• for the relief of occasional sleeplessness • reduces time to fall asleep if you have difficulty falling asleep

Warnings

Do not use • for children under 12 years of age • with any other product containing diphenhydramine, even one used on skin.

Ask a doctor before use if you have
• a breathing problem such as emphysema or chronic bronchitis • glaucoma
• difficulty in urination due to enlargement of the prostate gland

Ask a doctor or pharmacist before use if you are taking sedatives or tranquilizers

When using this product • avoid alcoholic beverages

Stop use and ask a doctor if sleeplessness persists continuously for more than 2 weeks. Insomnia may be a symptom of serious underlying medical illness.

PREGNANCY OR BREAST FEEDING

If pregnant or breast-feeding, ask a health professional before use.

Keep out of reach of children. In case of overdose, get medical help or contact a Poison Control Center right away. (1-800-222-1222)

Directions

take only one dose per day (24 hours)

adults & children 12 years & over | take 2 softgels at bedtime if needed or as directed by a doctor
children under 12 years | do not use

Other information

• store at 20-25° C (68-77° F) • avoid excessive heat above 40° C (104° F) and high humidity • Protect from light

Inactive ingredients

FD&C Blue#1, FD&C Red#40, gelatin, glycerin, polyethylene glycol, propylene glycol, purified water, sorbitol sorbitan solution, titanium dioxide

Questions or comments?

1-888-333-9792

Distributed By:
Spirit Pharmaceuticals, LLC
Ronkonkoma, NY 11779

Made in India